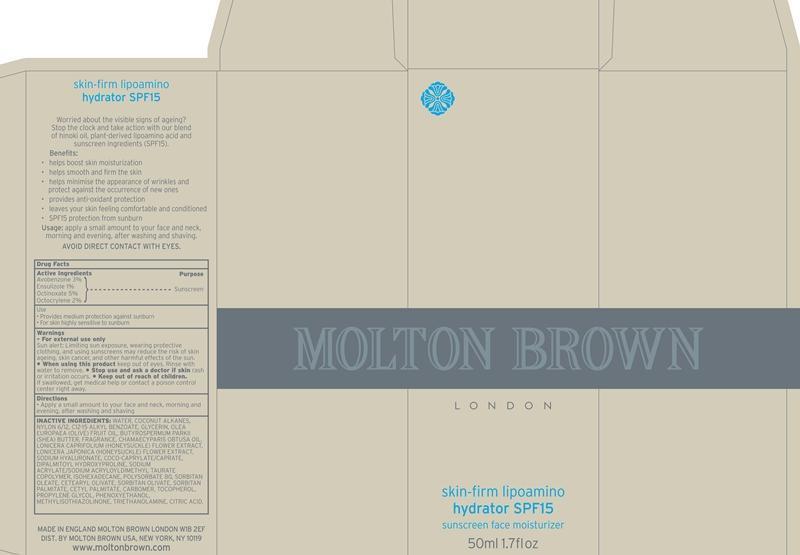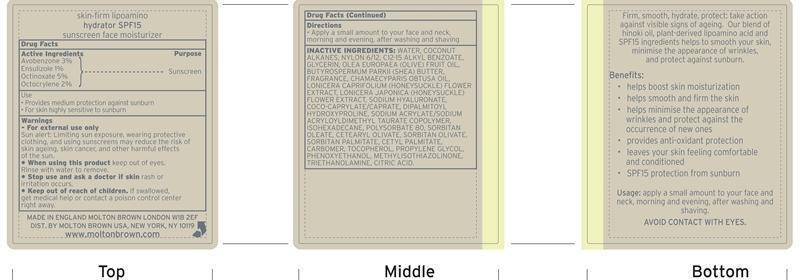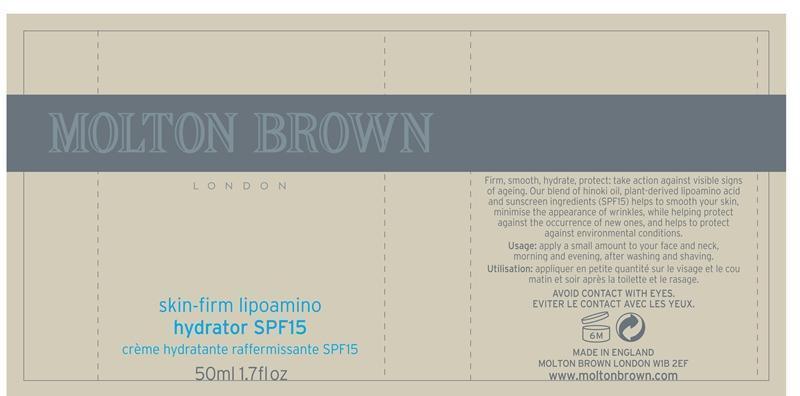 DRUG LABEL: Skin Firm Lipoamino hydrator SPF 15
NDC: 68814-250 | Form: LOTION
Manufacturer: Molton Brown LTD
Category: otc | Type: HUMAN OTC DRUG LABEL
Date: 20130404

ACTIVE INGREDIENTS: AVOBENZONE 3 g/100 mL; ENSULIZOLE 1 g/100 mL; OCTINOXATE 5 g/100 mL; OCTOCRYLENE 2 g/100 mL
INACTIVE INGREDIENTS: WATER; COCONUT ALKANES; ENSULIZOLE; ALKYL (C12-15) BENZOATE; GLYCERIN; OLIVE OIL; SHEA BUTTER; CHAMAECYPARIS OBTUSA WOOD OIL; LONICERA CAPRIFOLIUM FLOWER; LONICERA JAPONICA FLOWER; HYALURONATE SODIUM; COCO-CAPRYLATE/CAPRATE; DIPALMITOYL HYDROXYPROLINE; SODIUM ACRYLATE/SODIUM ACRYLOYLDIMETHYLTAURATE COPOLYMER (4000000 MW); ISOHEXADECANE; POLYSORBATE 80; SORBITAN MONOOLEATE; CETEARYL OLIVATE; SORBITAN OLIVATE; SORBITAN MONOPALMITATE; CETYL PALMITATE; CARBOMER 934; .ALPHA.-TOCOPHEROL; PROPYLENE GLYCOL; PHENOXYETHANOL; METHYLISOTHIAZOLINONE; TROLAMINE; CITRIC ACID MONOHYDRATE

Skin-firm Lipoamino Hydrator SPF15

Active Ingredients Purpose

Avobenzone 3% Sunscreen

Ensulizole 1% Sunscreen

Octinoxate 5% Sunscreen

Octocrylene 2% Sunscreen

Use

UseProvides medium protection against sunburn

For skin highly sensitive to sunburn

warning

Keep out of reach of children

Indications

Stop use and ask a doctor if skin rash or irritation occurs

warnings

For external use only

Sun alert: Limiting sun exposure, wearing protective clothing and using sunscreens may reduce the risk of skin ageing, skin cancer, and other harmful effects of the sun.

When using this product: Keep out of eyes. Rinse with water to remove.

If swallowed, get medical help or contact a poison control center right away.

Directions

Apply a small amount to your face and neck, morning and evening, after washing and shaving.

Inactive Ingredients

water, coconut alkanes, nylon 6/12, C12-15 alkyl benzoate, glycerin, olea europaea (olive) fruit oil, butyrospermum parkii (shea) butter, fragrance, chamaecyparis obtusa oil, lonicera caprifolium (honeysuckle) flower extract, lonicera japonica (honeysuckle) flower extract, sodium hyaluronate, coco-caprylate/caprate, dipalmitoyl hydroxyproline, sodium acrylate/sodium acryloyldimethyl taurate copolymer, isohexadecane, polysorbate 80, sorbitan oleate, cetearyl olivate, sorbitan palmitate, cetyl palmitate, carbomer, tocopherol, propylene glycol, phenoxyethanol, methylisothiazolinone, thriethanolamine, citric acid.

PACKAGE LABEL

Molton Brown

Skin Firm Lipoamino

hydrator SPF15

Moisturizing Sunscreen